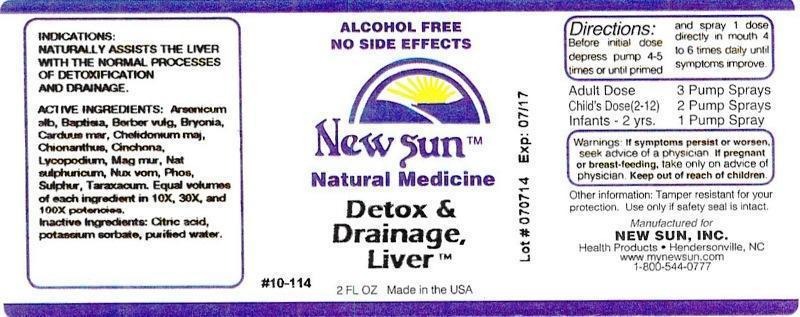 DRUG LABEL: Detox and Drainage, Liver
NDC: 66579-0014 | Form: LIQUID
Manufacturer: New Sun Inc.
Category: homeopathic | Type: HUMAN OTC DRUG LABEL
Date: 20140730

ACTIVE INGREDIENTS: ARSENIC TRIOXIDE 10 [hp_X]/59 mL; BAPTISIA TINCTORIA ROOT 10 [hp_X]/59 mL; BERBERIS VULGARIS ROOT BARK 10 [hp_X]/59 mL; BRYONIA ALBA ROOT 10 [hp_X]/59 mL; MILK THISTLE 10 [hp_X]/59 mL; CHELIDONIUM MAJUS 10 [hp_X]/59 mL; CHIONANTHUS VIRGINICUS BARK 10 [hp_X]/59 mL; CINCHONA OFFICINALIS BARK 10 [hp_X]/59 mL; LYCOPODIUM CLAVATUM SPORE 10 [hp_X]/59 mL; MANGANESE CHLORIDE 10 [hp_X]/59 mL; SODIUM SULFATE 10 [hp_X]/59 mL; STRYCHNOS NUX-VOMICA SEED 10 [hp_X]/59 mL; PHOSPHORUS 10 [hp_X]/59 mL; SULFUR 10 [hp_X]/59 mL; TARAXACUM OFFICINALE 10 [hp_X]/59 mL
INACTIVE INGREDIENTS: CITRIC ACID MONOHYDRATE; POTASSIUM SORBATE; WATER

Detox and Drainage, Liver

DOSAGE AND ADMINISTRATION

Directions: Before initial dose depress pump 4-5 times or until primed and spray 1 dose directly in mouth 4 to 6 times daily until symptoms improve.

Adult Dose: 3 Pump Sprays

Child's Dose (2-12): 2 Pump Sprays

Infants - 2 yrs: 1 Pump Spray

WARNINGS

Warnings: If symptoms persist or worsen, seek advice of physician. If pregnant or breast-feeding, take only on advice of physician.

Keep out of reach of children.

Other information: Tamper resistant for your protection. Use only if safety seal is intact.

PURPOSE

Indications: NATURALLY ASSISTS THE LIVER WITH THE NORMAL PROCESSES OF DETOXIFICATION AND DRAINAGE.

ACTIVE INGREDIENT

Active Ingredients: Arsenicum album, Baptisia tinctoria, Berberis vulgaris, Bryonia, Carduus marianus, Chelidonium majus, Chionanthus virginica, Cinchona officinalis, Lycopodium clavatum, Manganum muriaticum, Natrum sulphuricum, Nux vomica, Phosphorus, Sulphur, Taraxacum officinale. Equal volumes of each ingredient in 10X, 30X, 100X potencies.

Inactive Ingredient: Citric acid, potassium sorbate, purified water.

INDICATIONS AND USAGE

Indications: NATURALLY ASSISTS THE LIVER WITH THE NORMAL PROCESSES OF DETOXIFICATION AND DRAINAGE.